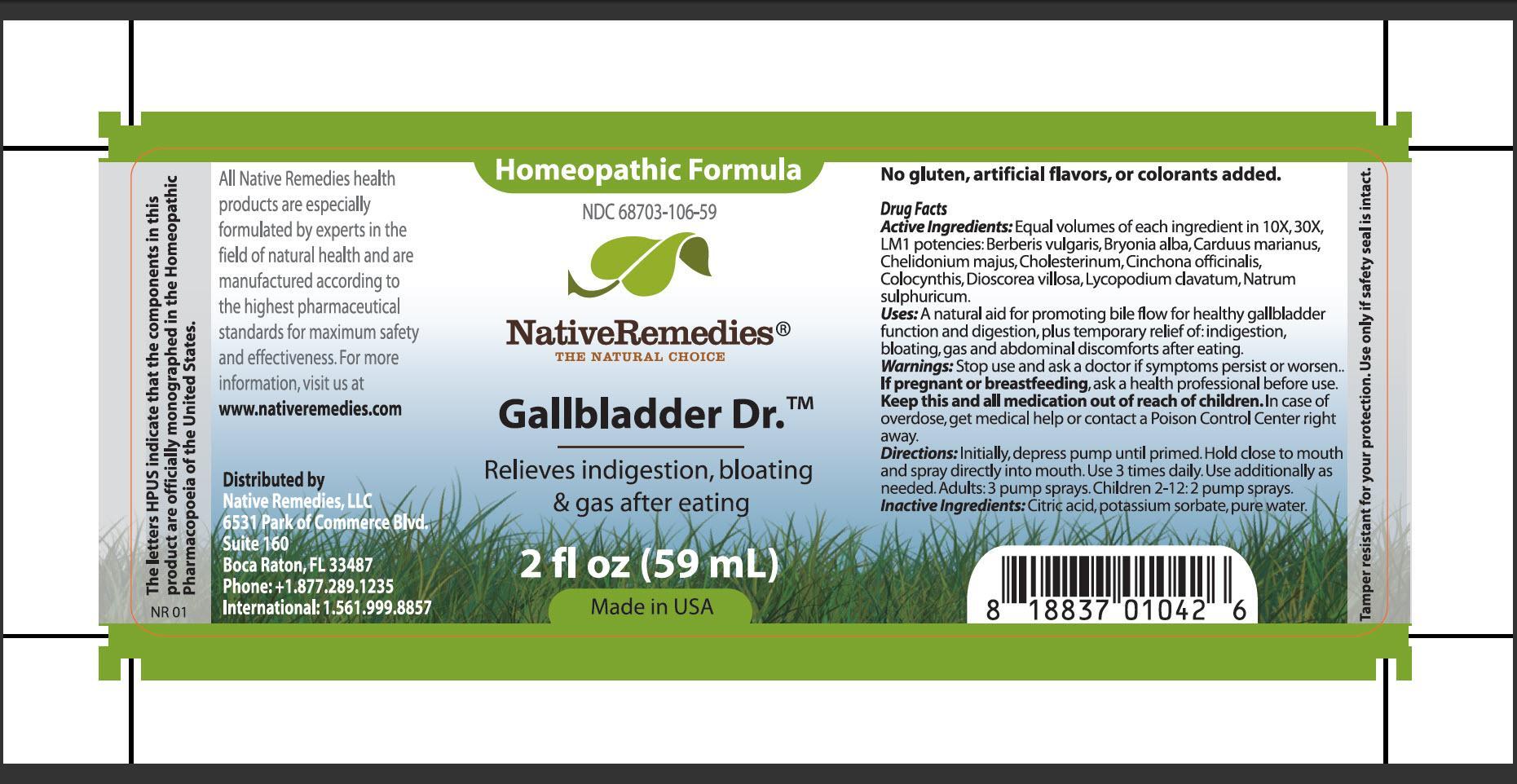 DRUG LABEL: Gallbladder Dr.
NDC: 68703-106 | Form: SPRAY
Manufacturer: Native Remedies, LLC
Category: homeopathic | Type: HUMAN OTC DRUG LABEL
Date: 20130722

ACTIVE INGREDIENTS: BERBERIS VULGARIS ROOT BARK 10 [hp_X]/59 mL; BRYONIA ALBA ROOT 10 [hp_X]/59 mL; SILYBUM MARIANUM SEED 10 [hp_X]/59 mL; CHELIDONIUM MAJUS 10 [hp_X]/59 mL; CHOLESTEROL 10 [hp_X]/59 mL; CINCHONA OFFICINALIS BARK 10 [hp_X]/59 mL; CITRULLUS COLOCYNTHIS FRUIT PULP 10 [hp_X]/59 mL; DIOSCOREA VILLOSA TUBER 10 [hp_X]/59 mL; LYCOPODIUM CLAVATUM SPORE 10 [hp_X]/59 mL; SODIUM SULFATE 10 [hp_X]/59 mL
INACTIVE INGREDIENTS: CITRIC ACID MONOHYDRATE; POTASSIUM SORBATE; WATER

Gallbladder Dr

PURPOSE

Relieves indigestion, bloating and gas after eating

Drug Facts
Active Ingredients: Equal volumes of each ingredient in 10X, 30X, LM1 potencies: Berberis vulgaris, Bryonia alba, Carduus marianus, Chelidonium majus, Cholesterinum, Chichona officinalis, Colocynthis, Dioscorea villosa, Lycopodium clavatum, Natrum sulphuricum

INDICATIONS AND USAGE

Uses: A natural aid for promoting bile flow for healthy gallbladder function and digestion, plus temporary relief of: indigestion, bloating, gas and abdominal discomforts after eating

WARNINGS

Warnings: Stop use and ask a doctor if symptoms persist or worsen

PREGNANCY OR BREAST FEEDING

If pregnant or breastfeeding, ask a health professional before use

KEEP OUT OF REACH OF CHILDREN

Keep this and all medication out of reach of children

OVERDOSAGE

In case of overdose, get medical help or contact a Poison Control Center right away

DOSAGE AND ADMINISTRATION

Directions: Initially, depress pump until primed. Hold close to mouth and spray directly into mouth. Use 3 times daily. Use additionally as needed. Adults: 3 pump sprays. Children 2-12: 2 pump sprays

Inactive Ingredients: Citric acid, potassium sorbate, pure water

PATIENT COUNSELING INFORMATION

The letters HPUS indicate that the components in this product are officially monographed in the Homeopathic Pharmacopoeia of the United States

All Native Remedies health products are especially formulated by experts in the field of natural health and are manufactured according to the highest pharmaceutical standards for maximum safety and effectiveness. For more information, visit us at www.nativeremedies.com

Distributed by
Native Remedies, LLC
6531 Park of Commerce Blvd.
Suite 160
Boca Raton, FL 33487
Phone: +1.877.289.1235
International: 1.561.999.8857

No gluten, artificial flavors, or colorants added

STORAGE AND HANDLING

Tamper resistant for your protection. Use only if safety seal is intact